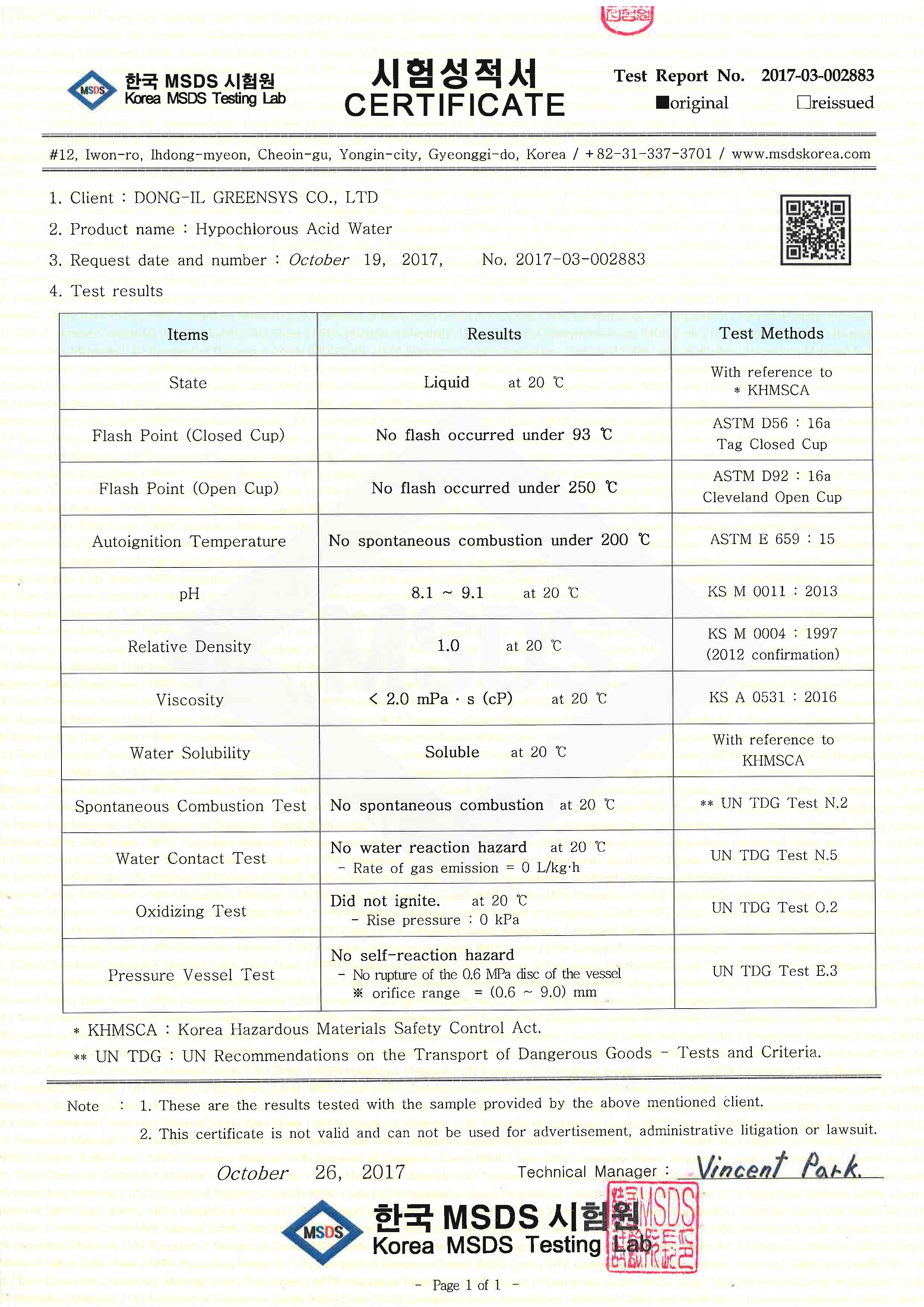 DRUG LABEL: Gold Mate
NDC: 72115-0001 | Form: LIQUID
Manufacturer: DONG-IL GREENSYS CO., LTD.
Category: otc | Type: HUMAN OTC DRUG LABEL
Date: 20180215

ACTIVE INGREDIENTS: HYPOCHLOROUS ACID 3 g/100 mL
INACTIVE INGREDIENTS: WATER; SODIUM CATION

Drug Facts

ACTIVE INGREDIENT

silymarin

INACTIVE INGREDIENT

vitamin B1, vitamin B2, vitamin B6, taurine, soybean lecithin, bee's wax, vitamin C, hovenia dulcis var koreana extract powder, lentinus edodes mycelia extract powder, basidio carp of ganoderma lucium extract powder, dandelion extract powder, nicotinic acid, folic acid

PURPOSE

sterilize and disinfect various pathogenic viruses

eliminate various bad smell and odor

keep out or reach of the children

INDICATIONS AND USAGE

washing and sterilization of hands

washing and sterilization of fruits, vegetables, and eggs

sterilization of refrigerators

sterilization and deodorization of living rooms and bed rooms including floors

WARNINGS

never drink the liquid

if the liquid gets into the eyes, do not rub eyes but immediately wash with flowing tab water

if skin is contacted with the undiluted liquid, immediately wash with flowing water

DOSAGE AND ADMINISTRATION

for home use only